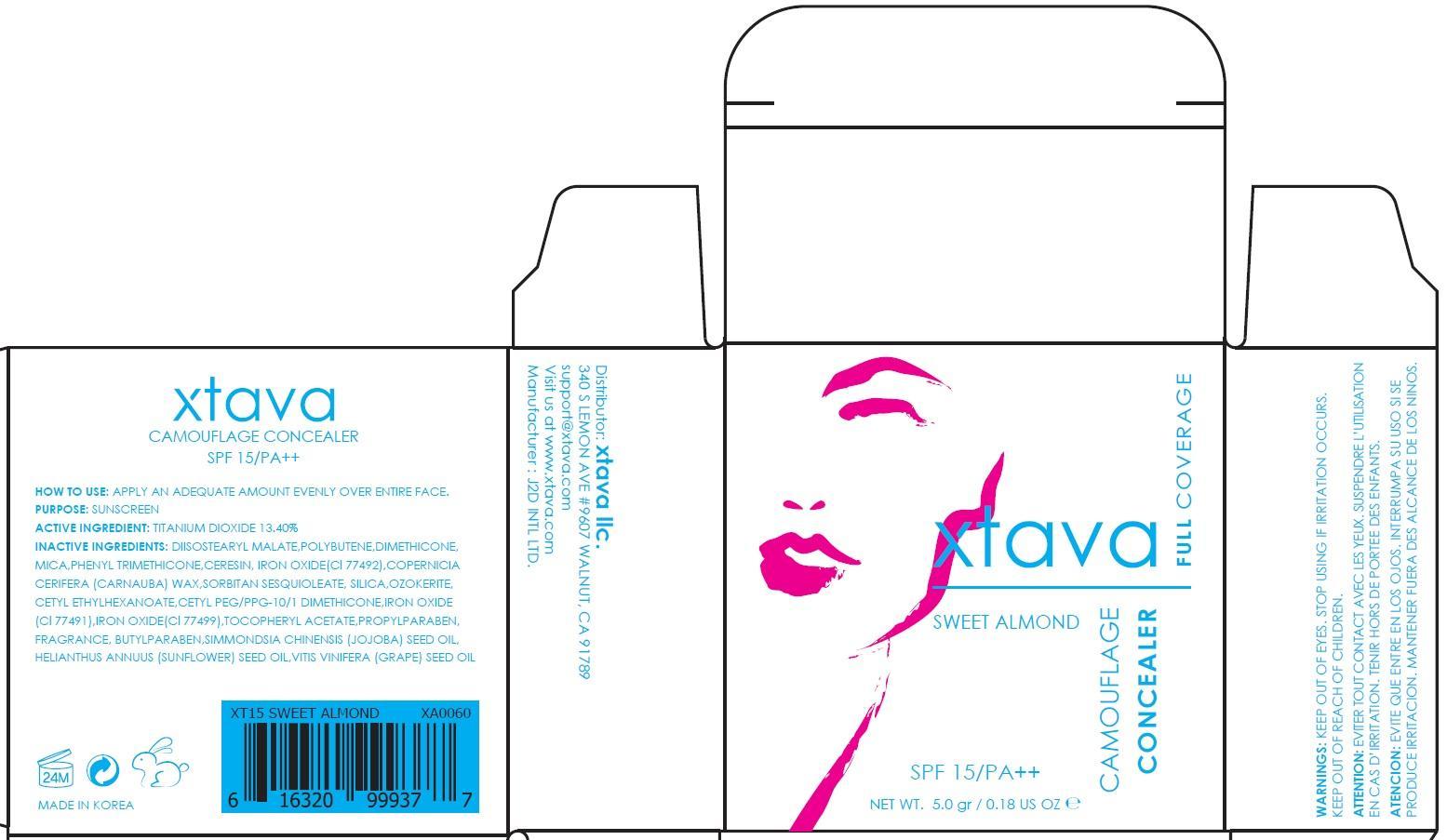 DRUG LABEL: CAMOUFLAGE CONCEALER SWEET ALMOND
NDC: 69958-060 | Form: POWDER
Manufacturer: J2D INTERNATIONAL
Category: otc | Type: HUMAN OTC DRUG LABEL
Date: 20150716

ACTIVE INGREDIENTS: Titanium Dioxide 0.67 g/5 g
INACTIVE INGREDIENTS: DIISOSTEARYL MALATE; DIMETHICONE

ACTIVE INGREDIENT

Active Ingredient: Titanium Dioxide 13.40%

INACTIVE INGREDIENT

Inactive Ingredients: DIISOSTEARYL MALATE, POLYBUTENE, DIMETHICONE, MICA, PHENYL TRIMETHICONE, CERESIN, IRON OXIDE(Cl 77492), COPERNICIA CERIFERA (CARNAUBA) WAX, SORBITAN SESQUIOLEATE, SILICA, OZOKERITE, CETYL ETHYLHEXANOATE, CETYL PEG/PPG-10/1 DIMETHICONE, IRON OXIDE(Cl 77491), IRON OXIDE(Cl 77499), TOCOPHERYL ACETATE, PROPYLPARABEN, PERFUME, BUTYLPARABEN, SIMMONDSIA CHINENSIS (JOJOBA) SEED OIL, HELIANTHUS ANNUUS (SUNFLOWER) SEED OIL, VITIS VINIFERA (GRAPE) SEED OIL

PURPOSE

Purpose: Sunscreen

WARNINGS

Warnings: KEEP OUT OF EYES. STOP USING IF IRRITATION OCCURS. KEEP OUT OF REACH OF CHILDREN.

DESCRIPTION

ATTENTION: EVITER TOUT CONTACT AVEC LES YEUX. SUSPENDRE L’UTILISATION EN CAS D’IRRITATION. TENIR HORS DE PORTEE DES ENFANTS.

ATENCION: EVITE QUE ENTRE EN LOS OJOS. INTERRUMPA SU USO SI SE PRODUCE IRRITACION. MANTENER FUERA DES ALCANCE DE LOS NINOS.

How to use: APPLY AN ADEQUATE AMOUNT EVENLY OVER ENTIRE FACE.